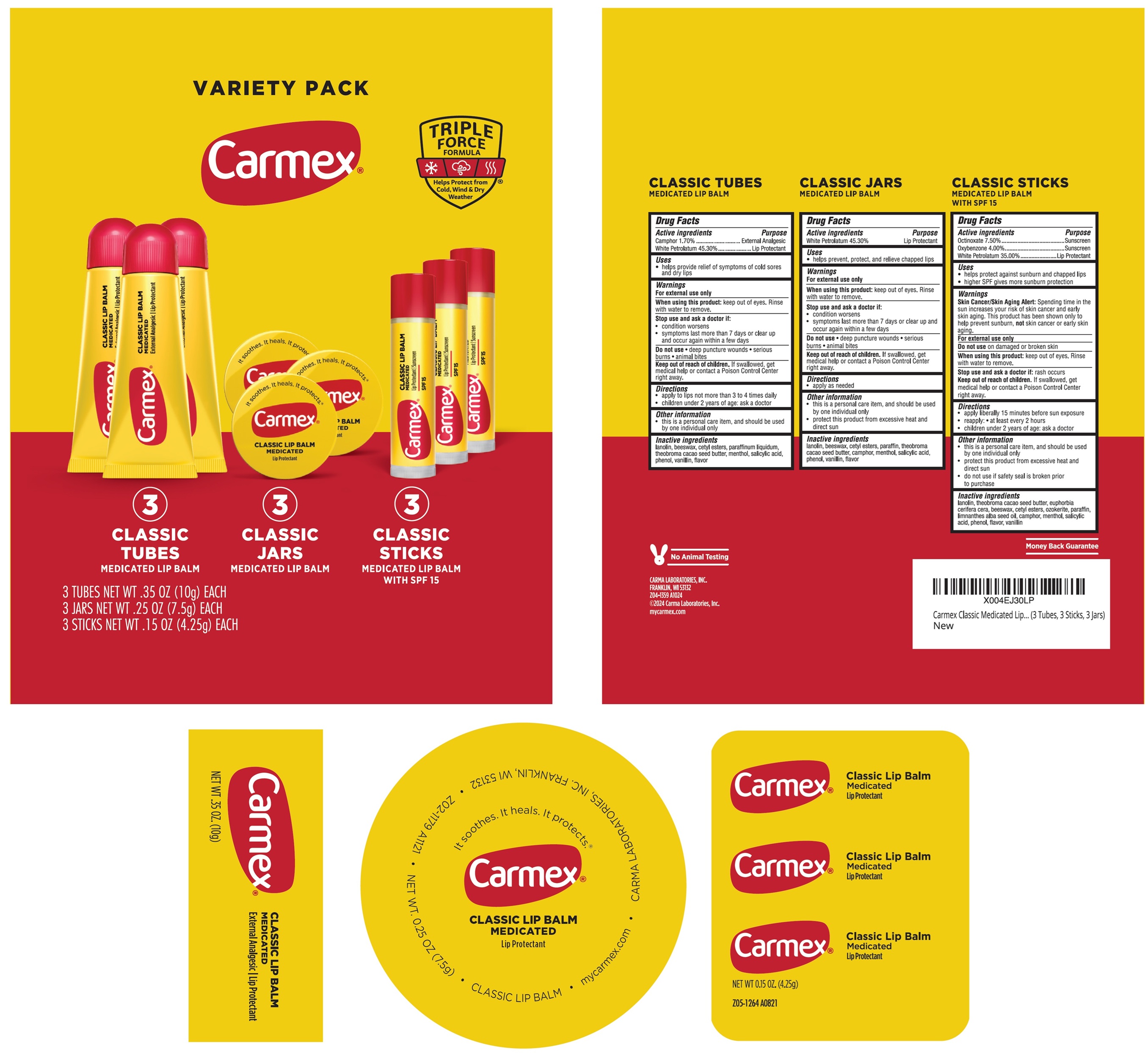 DRUG LABEL: Carmex Variety Pack Classic Medicated Lip Balm Lip Balm SPF 15
NDC: 10210-0089 | Form: KIT | Route: TOPICAL
Manufacturer: Carma Laboratories, Inc.
Category: otc | Type: HUMAN OTC DRUG LABEL
Date: 20250319

ACTIVE INGREDIENTS: CAMPHOR (SYNTHETIC) 1.7 g/100 g; WHITE PETROLATUM 45.3 g/100 g; OCTINOXATE 7.5 g/100 g; OXYBENZONE 4 g/100 g; WHITE PETROLATUM 35 g/100 g; WHITE PETROLATUM 453 mg/1 g
INACTIVE INGREDIENTS: LANOLIN; YELLOW WAX; CETYL ESTERS WAX; MINERAL OIL; MENTHOL, UNSPECIFIED FORM; SALICYLIC ACID; PHENOL; VANILLIN; COCOA BUTTER; LANOLIN; YELLOW WAX; CETYL ESTERS WAX; PARAFFIN; MEADOWFOAM SEED OIL; CAMPHOR (SYNTHETIC); MENTHOL, UNSPECIFIED FORM; SALICYLIC ACID; PHENOL; VANILLIN; LANOLIN; YELLOW WAX; CETYL ESTERS WAX; PARAFFIN; MEADOWFOAM SEED OIL; CAMPHOR (SYNTHETIC); MENTHOL, UNSPECIFIED FORM; SALICYLIC ACID; PHENOL; VANILLIN

Carmex Variety Pack Classic Medicated Lip Balm Lip Balm SPF 15

Active ingredients

Camphor 1.70%

White Petrolatum 45.30%

Purpose

External Analgesic

Lip Protectant

Uses

- helps provide relief of symptoms of cold sores and dry lips

Warnings

For external use only

When using this product:

keep out of eyes. Rinse with water to remove.

Stop use and ask a doctor if:

- condition worsens
- symptoms last more than 7 days or clear up and occur again within a few days

Do not use

- deep puncture wounds
- serious burns
- animal bites

Keep out of reach of children.

If swallowed, get medical help or contact a Poison Control Center right away.

Directions

• apply to lips not more than 3 to 4 times daily

• children under 2 years of age: ask a doctor

Other information

• this is a personal care item, and should be used by one individual only

Inactive ingredients

lanolin, beeswax, cetyl esters, paraffinum liquidum, theobroma cacao seed butter, menthol, salicylic acid, phenol, vanillin, flavor

Active ingredients

Octinoxate 7.50%

Oxybenzone 4.00%

White Petrolatum 35.00%

Purpose

Sunscreen

Lip Protectant

Uses

- helps protect against sunburn and chapped lips
- higher SPF gives more sunburn protection

Warnings

Skin Cancer/Skin Aging Alert: Spending time in the sun increases your risk of skin cancer and early skin aging. This product has been shown only to help prevent sunburn, not skin cancer or early skin aging.

For external use only

Do not use

on damaged or broken skin

When using this product:

keep out of eyes. Rinse with water to remove.

Stop use and ask a doctor if:

rash occurs

Keep out of reach of children.

If swallowed, get medical help or contact a Poison Control Center right away.

Directions

• apply liberally 15 minutes before sun exposure

• reapply: • at least every 2 hours

• children under 2 years of age: ask a doctor

Other information

• this is a personal care item, and should be used by one individual only

• protect this product from excessive heat and direct sun

• do not use if safety seal is broken prior to purchase

Inactive ingredients

lanolin, theobroma cacao seed butter, euphorbia cerifera cera, beeswax, cetyl esters, ozokerite, paraffin, limnanthes alba seed oil, camphor, menthol, salicylic acid, phenol, flavor, vanillin

Active ingredients

White Petrolatum 45.30%

Purpose

Lip Protectant

Uses

- helps prevent, protect, and relieve chapped lips

Warnings

For external use only

When using this product:

keep out of eyes. Rinse with water to remove.

Stop use and ask a doctor if:

- condition worsens
- symptoms last more than 7 days or clear up and occur again within a few days

Do not use

- deep puncture wounds
- serious burns
- animal bites

Keep out of reach of children.

If swallowed, get medical help or contact a Poison Control Center right away.

Directions

- apply as needed

Other information

- this is a personal care item, and should be used by one individual only
- protect this product from excessive heat and direct sun

Inactive ingredients

lanolin, beeswax, cetyl esters, paraffin, theobroma cacao seed butter, camphor, menthol, salicylic acid, phenol, vanillin, flavor